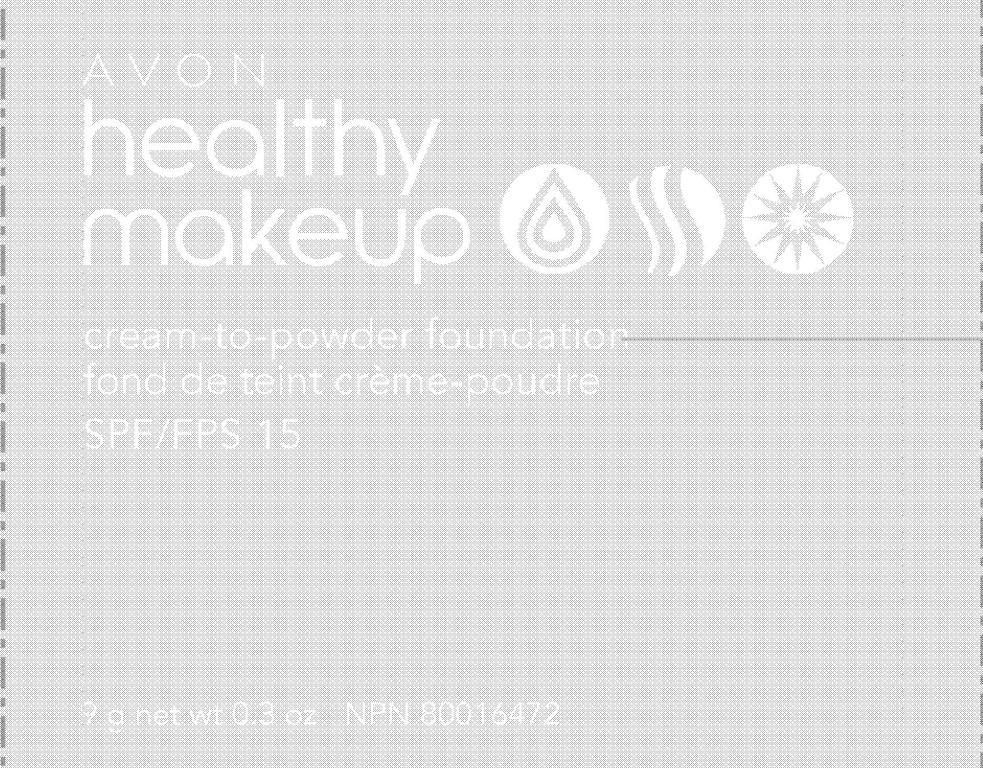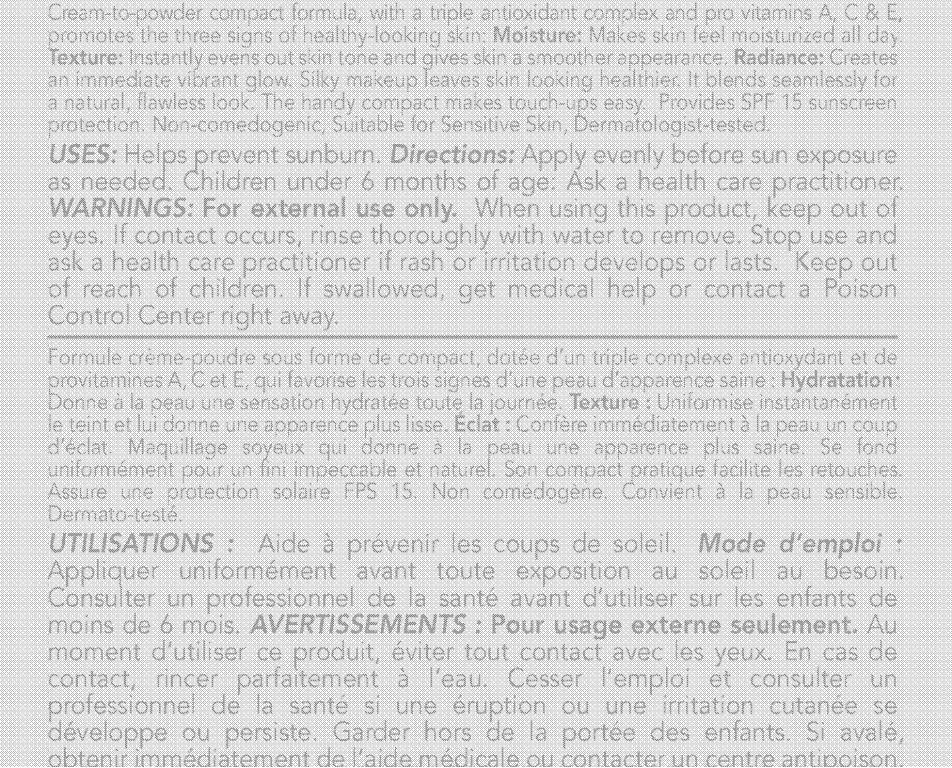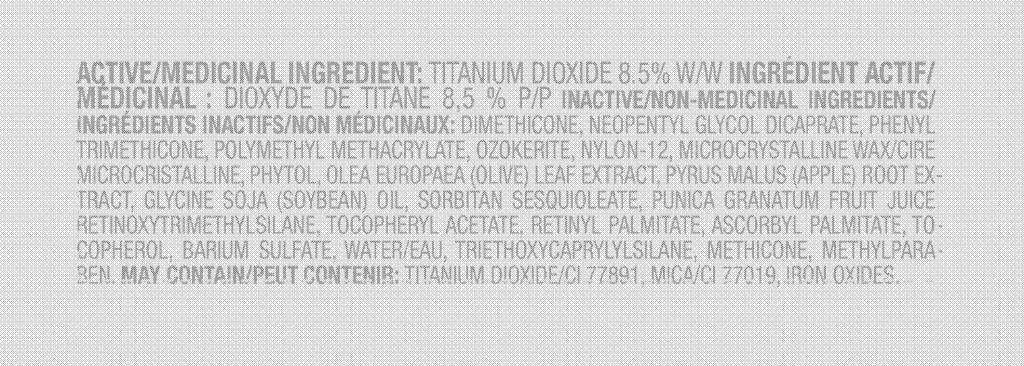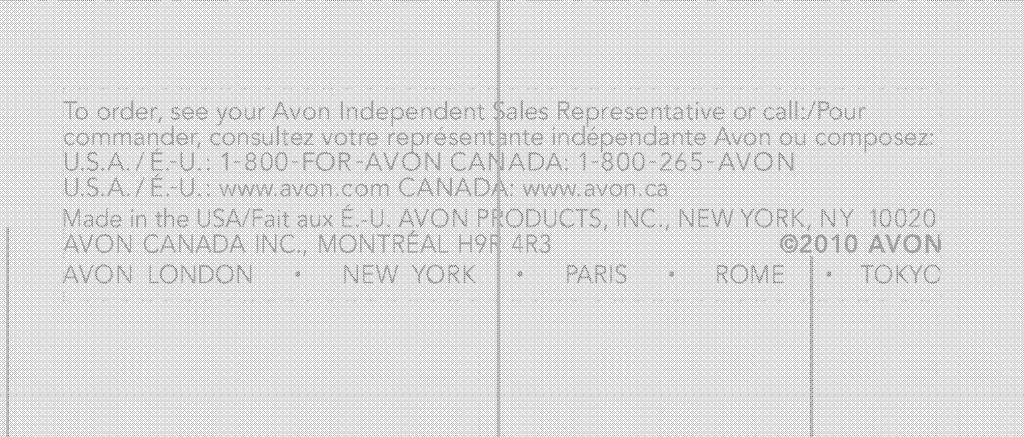 DRUG LABEL: Healthy Makeup
NDC: 10096-0214 | Form: CREAM
Manufacturer: Avon Products, Inc.
Category: otc | Type: HUMAN OTC DRUG LABEL
Date: 20100609

ACTIVE INGREDIENTS: TITANIUM DIOXIDE 765 mg/9 g
INACTIVE INGREDIENTS: DIMETHICONE; PHENYL TRIMETHICONE; SORBITAN SESQUIOLEATE; ASCORBYL PALMITATE; BARIUM SULFATE; WATER; METHYLPARABEN; TITANIUM DIOXIDE; MICA

INDICATIONS AND USAGE

Uses: Helps prevent sunburn.

DOSAGE AND ADMINISTRATION

Directions: Apply evenly before sun exposure as needed. Children under 6 months of age: Ask a healthcare practitioner.

WARNINGS: For external use only.

When using this product, keep out of eyes. If contact occurs, rinse thoroughly with water to remove.

Stop use and ask a health care practitioner if rash or irritation develops or lasts.

Keep out of reach of children. If swallowed, get medical help or contact a Poison Control Center right away.

Active/Medicinal Ingredient: TITANIUM DIOXIDE 8.5%

Inactive/Non Medicinal Ingredients:

DIMETHICONE
NEOPENTYL GLYCOL DICAPRATE
PHENYL TRIMETHICONE
POLYMETHYL METHACRYLATE
OZOKERITE
NYLON-12
MICROCRYSTALLINE WAX/CIRE MICROCRISTALLINE
PHYTOL
OLEA EUROPAEA (OLIVE) LEAF EXTRACT
PYRUS MALUS (APPLE) ROOT EXTRACT
GLYCINE SOJA (SOYBEAN) OIL
SORBITAN SESQUIOLEATE
PUNICA GRANATUM FRUIT JUICE
RETINOXYTRIMETHYLSILANE
TOCOPHERYL ACETATE
RETINYL PALMITATE
ASCORBYL PALMITATE
TOCOPHEROL
BARIUM SULFATE
WATER/EAU
TRIETHOXYCAPRYLYLSILANE
METHICONE
METHYLPARABEN
MAY CONTAIN:
TITANIUM DIOXIDE/CI 77891
MICA/CI 77019
IRON OXIDES